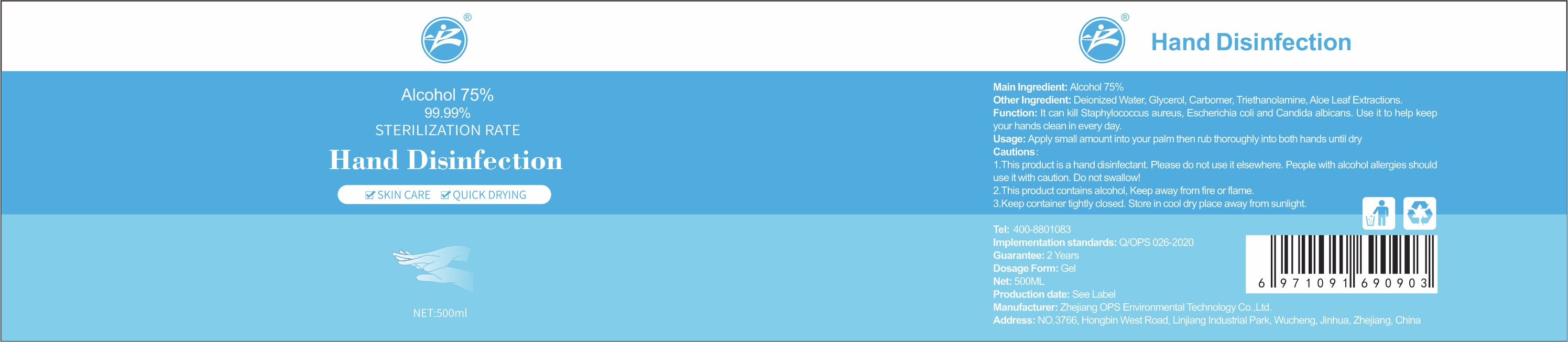 DRUG LABEL: Hand Disinfection
NDC: 55059-001 | Form: GEL
Manufacturer: Zhe Jiang OPS Environmental Technology Co.,Ltd.
Category: otc | Type: HUMAN OTC DRUG LABEL
Date: 20200510

ACTIVE INGREDIENTS: ALCOHOL 375 mL/500 mL
INACTIVE INGREDIENTS: CARBOMER HOMOPOLYMER, UNSPECIFIED TYPE; WATER; TROLAMINE; GLYCERIN; ALOE VERA LEAF

DOSAGE AND ADMINISTRATION

Keep container tightly closed. Store in cool dry place away from sunlight.

INACTIVE INGREDIENT

Deionized Water, Glycerol, Carbomer, Triethanolamine，Aloe Leaf Extractions

INDICATIONS AND USAGE

Apply small amount into your palm then rub thoroughly into both hands until dry.

ACTIVE INGREDIENT

Alcohol

keep out of reach of children

PURPOSE

Disinfection
Sterilization
No Rinseing

WARNINGS

1.This product is a hand disinfectant. Please do not use it elsewhere. People with alcohol allergies should use it with caution. Do not swallow!
2.This product contains alcohol, Keep away from fire or flame.
3.Keep container tightly closed. Store in cool dry place away from sunlight.